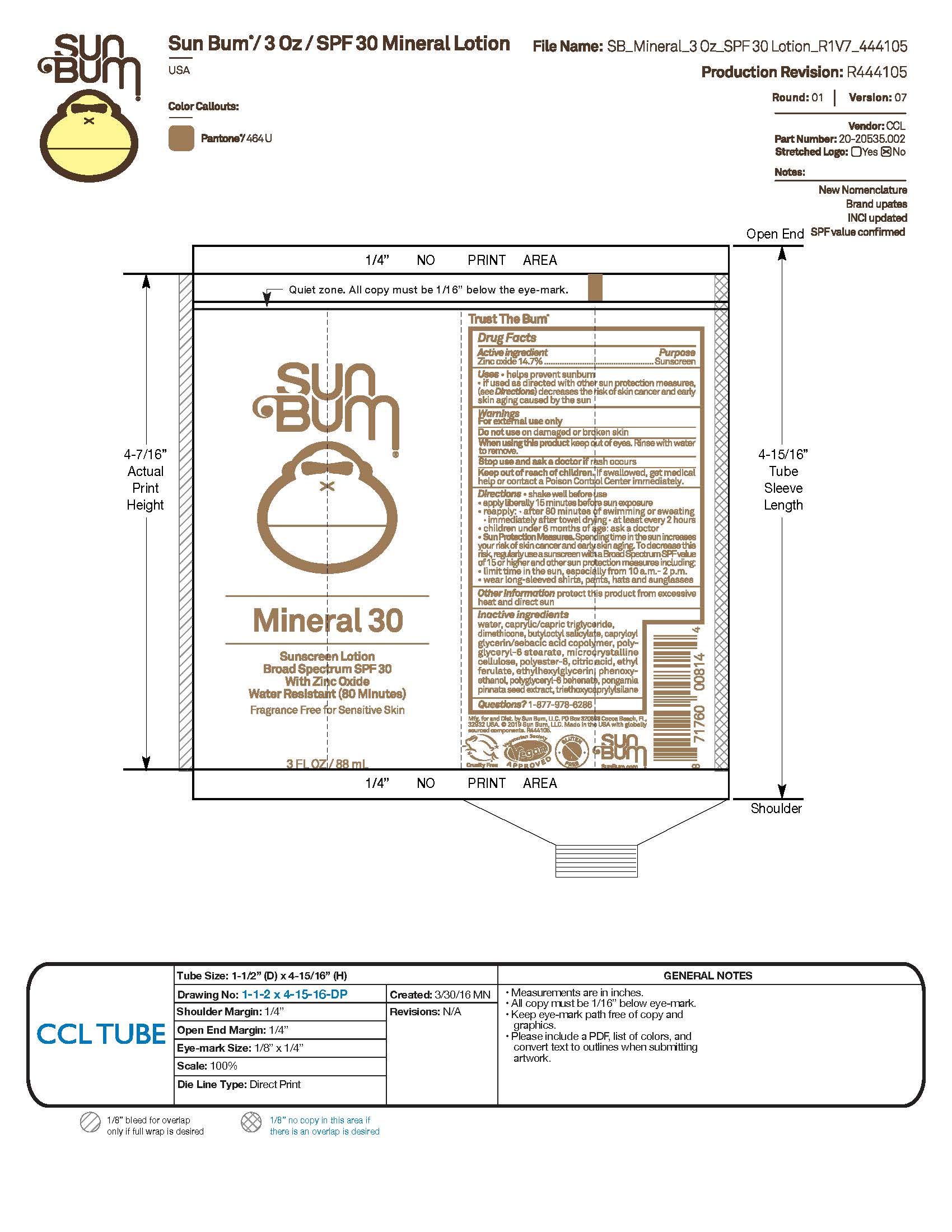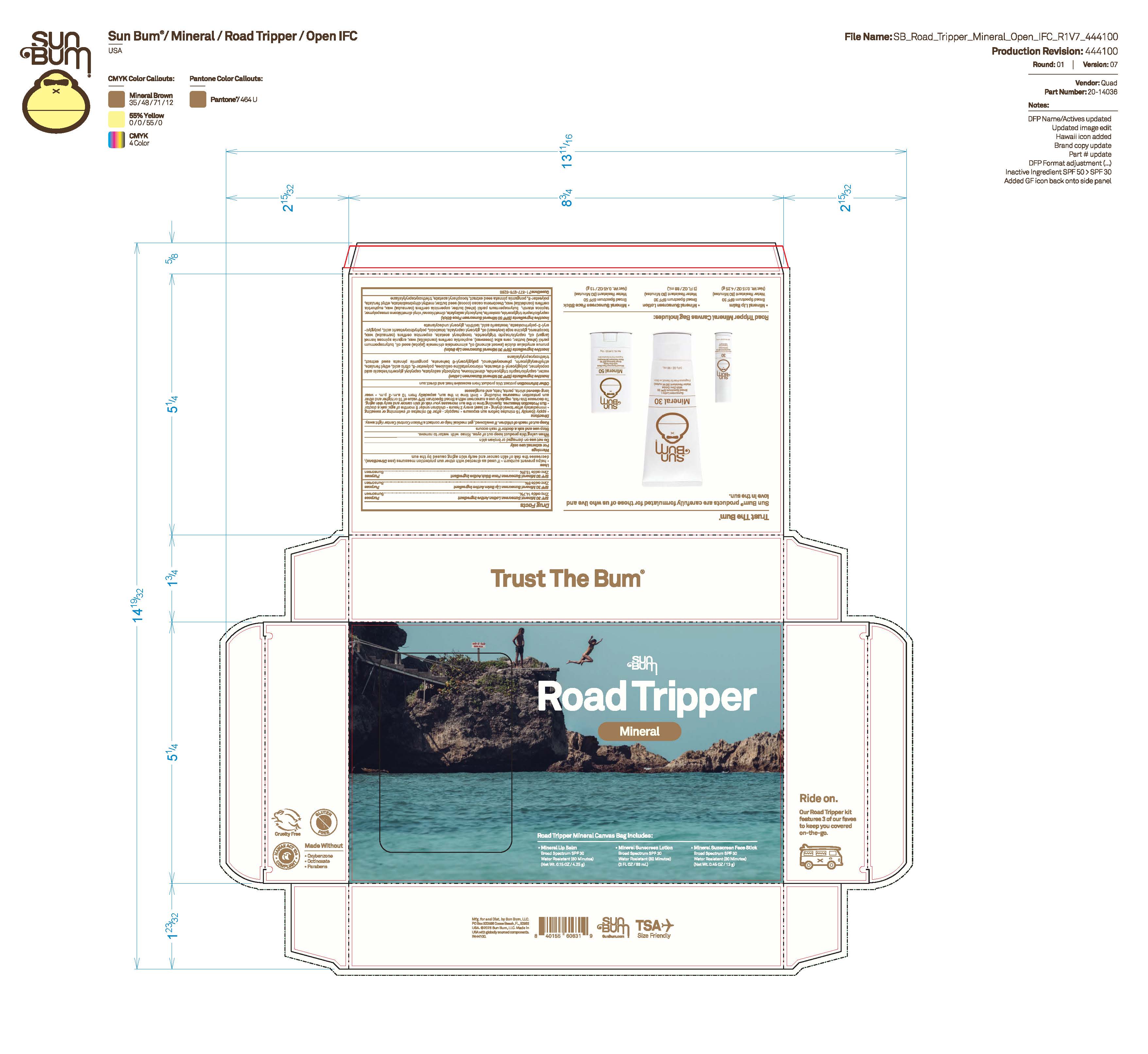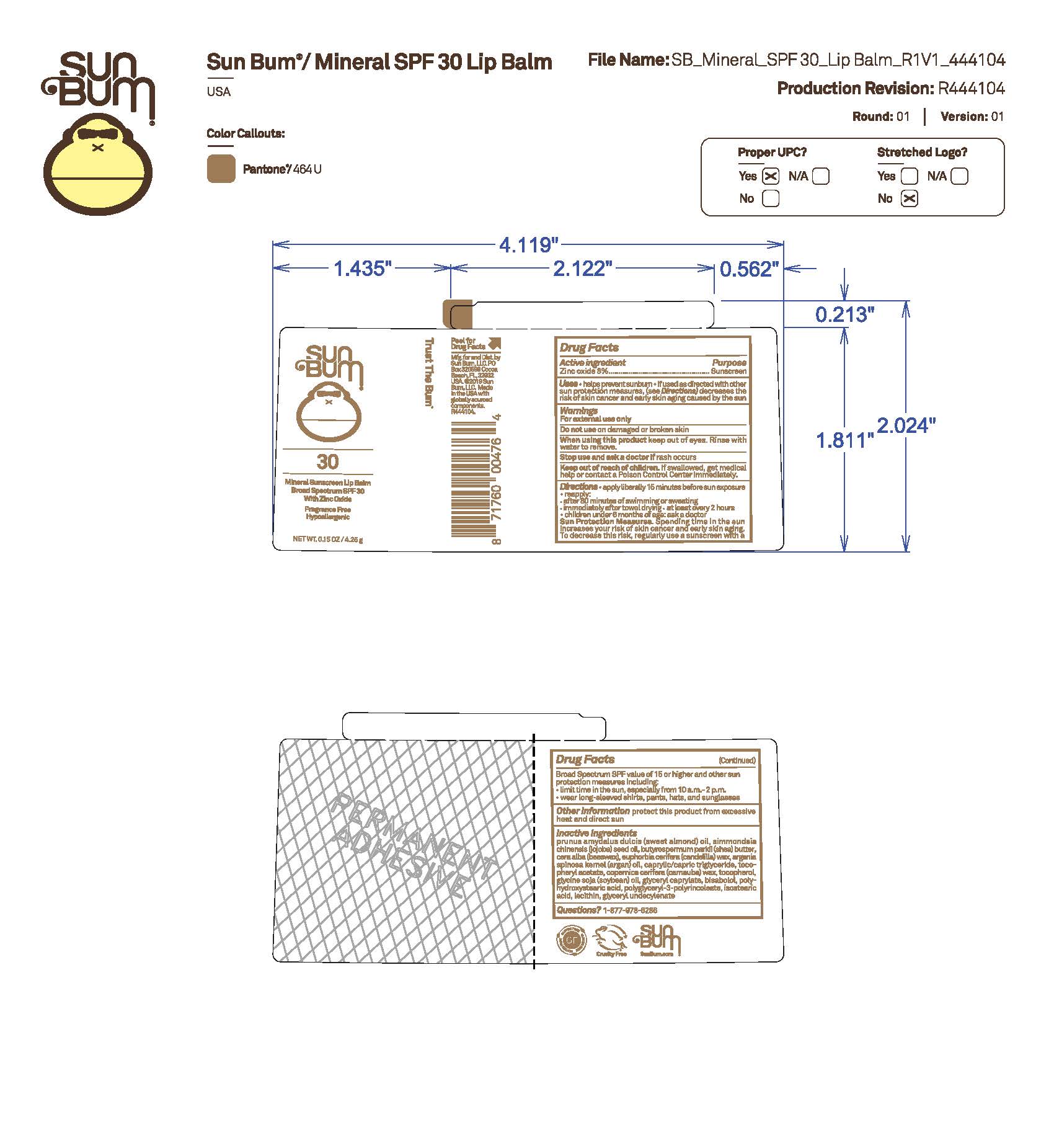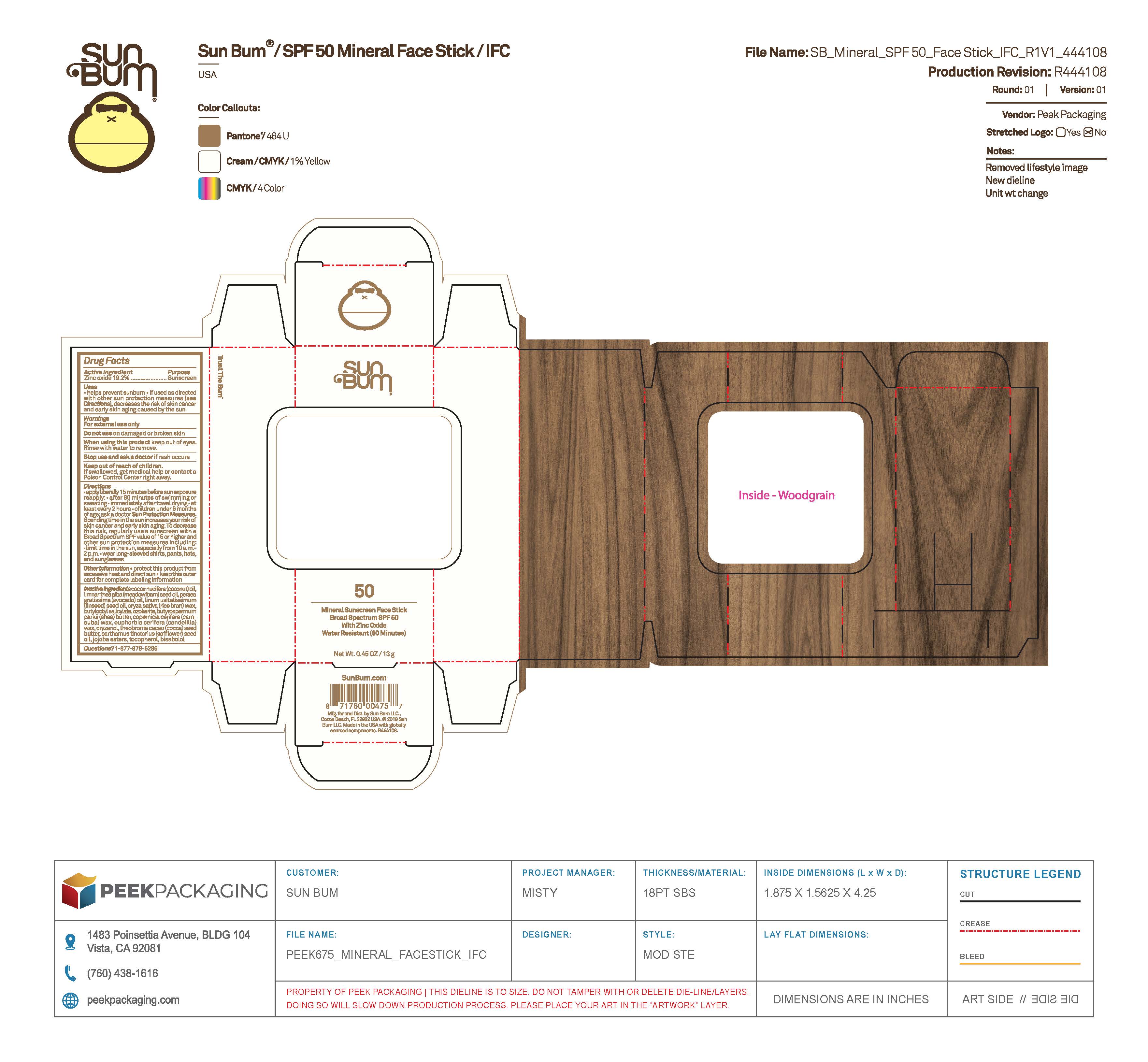 DRUG LABEL: Sun Bum Road Tripper Mineral - Mineral Sunscreen Face Stick Broad Spectrum SPF 50
NDC: 69039-773 | Form: STICK
Manufacturer: Sun Bum, LLC
Category: otc | Type: HUMAN OTC DRUG LABEL
Date: 20250902

ACTIVE INGREDIENTS: ZINC OXIDE 138 mg/1 g
INACTIVE INGREDIENTS: BUTYLOCTYL SALICYLATE; COPERNICIA CERIFERA (CARNAUBA) WAX; ETHYL FERULATE; CERESIN; PONGAMIA PINNATA SEED; TRIETHOXYCAPRYLYLSILANE; BUTYROSPERMUM PARKII (SHEA) BUTTER; POLYESTER-8 (1400 MW, CYANODIPHENYLPROPENOYL CAPPED); CAPRYLIC/CAPRIC TRIGLYCERIDE; .ALPHA.-TOCOPHEROL ACETATE; METHYL DIHYDROABIETATE; DIMETHICONE/VINYL DIMETHICONE CROSSPOLYMER (SOFT PARTICLE); TAPIOCA STARCH; EUPHORBIA CERIFERA (CANDELILLA) WAX; THEOBROMA CACAO (COCOA) SEED BUTTER

Sun Bum Road Tripper Mineral - Sunscreen, Lip Balm, Face Stick

Sun Bum Road Tripper Mineral - Mineral Sunscreen Broad Spectrum SPF 30 Active Ingredients

Zinc Oxide 14.7%

Sun Bum Road Tripper Mineral - Mineral Lip Balm Broad Spectrum SPF 30 Active Ingredients

Zinc Oxide 8%

Sun Bum Road Tripper Mineral - Mineral Sunscreen Face Stick Broad Spectrum SPF 50 Active Ingredients

Zinc Oxide 13.8%

Purpose

Sunscreen

Uses

• helps prevent sunburn • if used as directed with other sun protection measures, (see Directions) decreases the risk of skin cancer and early skin aging caused by the sun

Warnings

For external use only

Do not use on damaged or broken skin

When using this product keep out of eyes. Rinse with water to remove.

Stop use and ask a doctor if rash occurs

Keep out of reach of children. If swallowed, get medical help or contact a Poison Control Center immediately.

Warnings

Keep Out Of Reach Of Children

Directions

• apply liberally 15 minutes before sun exposure

• reapply: • after 80 minutes of swimming or sweating • immediately after towel drying • at least every 2 hours

• children under 6 months of age: ask a doctor

• Sun Protection Measures. Spending time in the sun increases your risk of skin cancer and early skin aging. To decrease this risk, regularly use a sunscreen with a Broad Spectrum SPF value of 15 or higher and other sun protection measures including:

• limit time in the sun, especially from 10 a.m.- 2 p.m.

• wear long-sleeved shirts, pants, hats and sunglasses

Directions

• apply liberally 15 minutes before sun exposure

Other Information

protect this product from excessive heat and direct sun

Sun Bum Road Tripper Mineral - Mineral Sunscreen Broad Spectrum SPF 30 Inactive Ingredients

WATER, CAPRYLIC/CAPRIC TRIGLYCERIDE, DIMETHICONE, BUTYLOCTYL SALICYLATE, CAPRYLOYL GLYCERIN/SEBACIC ACID COPOLYMER, POLYGLYCERYL-6 STEARATE, MICROCRYSTALLINE CELLULOSE, POLYESTER-8, CITRIC ACID, ETHYL FERULATE, ETHYLHEXYLGLYCERIN, PHENOXYETHANOL, POLYGLYCERYL-6 BEHENATE, PONGAMIA PINNATA SEED EXTRACT, TRIETHOXYCAPRYLYLSILANE

Sun Bum Road Tripper Mineral - Mineral Lip Balm Broad Spectrum SPF 30 Inactive Ingredients

PRUNUS AMYGDALUS DULCIS (SWEET ALMOND) OIL, SIMMONDSIA CHINENSIS (JOJOBA) SEED OIL, BUTYROSPERMUM PARKII (SHEA) BUTTER, BEESWAX, EUPHORBIA CERIFERA (CANDELILLA) WAX, ARGANIA SPINOSA KERNEL (ARGAN) OIL, CAPRYLIC/CAPRIC TRIGLYCERIDE, TOCOPHEROL ACETATE, COPERNICIA CERIFERA (CARNAUBA) WAX, TOCOPHEROL, GLYCINE SOJA (SOYBEAN) OIL, GLYCERYL CAPRYLATE, BISABOLOL, POLYHYDROXYSTEARIC ACID, POLYGLYCERYL-3-POLYRINCOLEATE, ISOSTEARIC ACID, LECITHIN, GLYCERYL UNDECYLENATE

Sun Bum Road Tripper Mineral - Mineral Sunscreen Face Stick Broad Spectrum SPF 50 Inactive Ingredients

CAPRYLIC/CAPRIC TRIGLYCERIDE, OZOKERITE, BUTYLOCTYL SALICYLATE, DIMETHICONE/VINYL DIMETHICONE CROSSPOLYMER, TAPIOCA STARCH, BUTYROSPERMUM PARKII (SHEA) BUTTER, COPERNICIA CERIFERA (CARNAUBA) WAX, EUPHORBIA CERIFERA (CANDELILLA) WAX, THEOBROMA CACAO (COCOA) SEED BUTTER, METHYL DIHYDROABIETATE, ETHYL FERULATE, POLYESTER-8, PONGAMIA PINNATA SEED EXTRACT, TOCOPHEROL ACETATE, TRIETHOXYCAPRYLYLSILANE

Questions?

1-877-978-6286